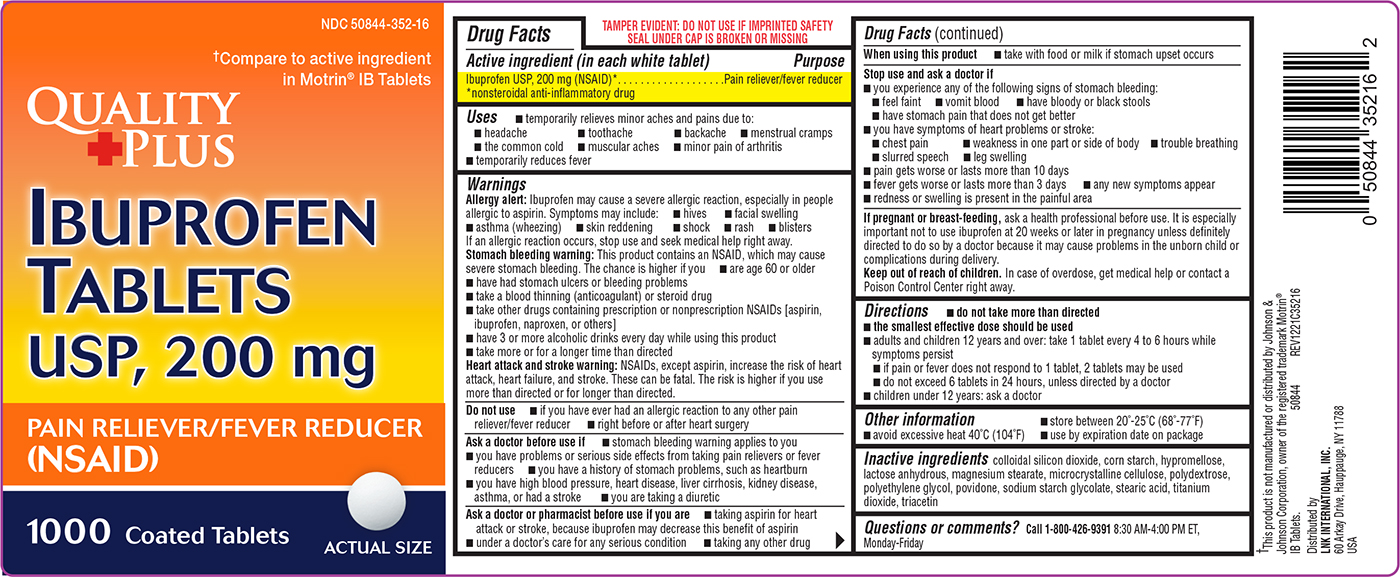 DRUG LABEL: Ibuprofen
NDC: 50844-352 | Form: TABLET, FILM COATED
Manufacturer: L.N.K. International, Inc.
Category: otc | Type: HUMAN OTC DRUG LABEL
Date: 20260113

ACTIVE INGREDIENTS: IBUPROFEN 200 mg/1 1
INACTIVE INGREDIENTS: SILICON DIOXIDE; STARCH, CORN; HYPROMELLOSE, UNSPECIFIED; ANHYDROUS LACTOSE; MAGNESIUM STEARATE; MICROCRYSTALLINE CELLULOSE; POLYDEXTROSE; POLYETHYLENE GLYCOL, UNSPECIFIED; POVIDONE, UNSPECIFIED; SODIUM STARCH GLYCOLATE TYPE A POTATO; STEARIC ACID; TITANIUM DIOXIDE; TRIACETIN

Quality Plus 44-352

Active ingredient (in each white tablet)

Ibuprofen USP, 200 mg (NSAID)*
*nonsteroidal anti-inflammatory drug

Purpose

Pain reliever/fever reducer

Uses

- temporarily relieves minor aches and pains due to:
  - headache
  - toothache
  - backache
  - menstrual cramps
  - the common cold
  - muscular aches
  - minor pain of arthritis
- temporarily reduces fever

Warnings

Allergy alert: Ibuprofen may cause a severe allergic reaction, especially in people allergic to aspirin. Symptoms may include:

- hives
- facial swelling
- asthma (wheezing)
- skin reddening
- shock
- rash
- blisters

If an allergic reaction occurs, stop use and seek medical help right away.

Stomach bleeding warning: This product contains an NSAID, which may cause severe stomach bleeding. The chance is higher if you

- are age 60 or older
- have had stomach ulcers or bleeding problems
- take a blood thinning (anticoagulant) or steroid drug
- take other drugs containing prescription or nonprescription NSAIDs [aspirin, ibuprofen, naproxen, or others]
- have 3 or more alcoholic drinks every day while using this product
- take more or for a longer time than directed

Heart attack and stroke warning: NSAIDs, except aspirin, increase the risk of heart attack, heart failure, and stroke. These can be fatal. The risk is higher if you use more than directed or for longer than directed.

Do not use

- if you have ever had an allergic reaction to any other pain reliever/fever reducer
- right before or after heart surgery

Ask a doctor before use if

- stomach bleeding warning applies to you
- you have problems or serious side effects from taking pain relievers or fever reducers
- you have a history of stomach problems, such as heartburn
- you have high blood pressure, heart disease, liver cirrhosis, kidney disease, asthma, or had a stroke
- you are taking a diuretic

Ask a doctor or pharmacist before use if you are

- taking aspirin for heart attack or stroke, because ibuprofen may decrease this benefit of aspirin
- under a doctor’s care for any serious condition
- taking any other drug

When using this product

- take with food or milk if stomach upset occurs

Stop use and ask a doctor if

- you experience any of the following signs of stomach bleeding:
  - feel faint
  - vomit blood
  - have bloody or black stools
  - have stomach pain that does not get better
- you have symptoms of heart problems or stroke:
  - chest pain
  - weakness in one part or side of body
  - leg swelling
  - slurred speech
  - trouble breathing
- pain gets worse or lasts more than 10 days
- fever gets worse or lasts more than 3 days
- any new symptoms appear
- redness or swelling is present in the painful area

If pregnant or breast-feeding,

ask a health professional before use. It is especially important not to use ibuprofen at 20 weeks or later in pregnancy unless definitely directed to do so by a doctor because it may cause problems in the unborn child or complications during delivery.

Keep out of reach of children.

In case of overdose, get medical help or contact a Poison Control Center right away.

Directions

- do not take more than directed
- the smallest effective dose should be used
- adults and children 12 years and over: take 1 tablet every 4 to 6 hours while symptoms persist
  - if pain or fever does not respond to 1 tablet, 2 tablets may be used
  - do not exceed 6 tablets in 24 hours, unless directed by a doctor
- children under 12 years: ask a doctor

Other information

- store between 20°-25°C (68°-77°F)
- avoid excessive heat 40°C (104°F)
- use by expiration date on package

Inactive ingredients

colloidal silicon dioxide, corn starch, hypromellose, lactose anhydrous, magnesium stearate, microcrystalline cellulose, polydextrose, polyethylene glycol, povidone, sodium starch glycolate, stearic acid, titanium dioxide, triacetin

Questions or comments?

Call 1-800-426-9391 8:30 AM-4:00 PM ET, Monday-Friday

Principal Display Panel

Quality
+Plus

NDC 50844-352-16

†Compare to active ingredient
in Motrin® IB Tablets

IBUPROFEN
TABLETS
USP, 200 mg

PAIN RELIEVER/FEVER REDUCER
(NSAID)

1000 Coated Tablets

ACTUAL SIZE

TAMPER EVIDENT: DO NOT USE IF IMPRINTED SAFETY
SEAL UNDER CAP IS BROKEN OR MISSING

†This product is not manufactured or distributed by Johnson &
Johnson Corporation, owner of the registered trademark Motrin®
IB Tablets. 50844 REV1221C35216

Distributed by
LNK INTERNATIONAL, INC.
60 Arkay Drive, Hauppauge, NY 11788
USA

Quality Plus 44-352